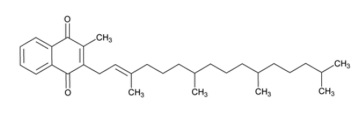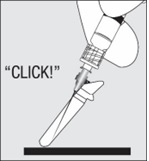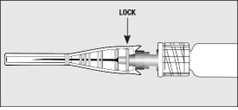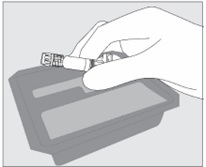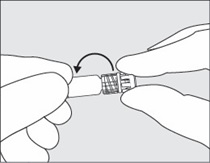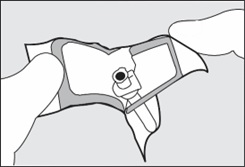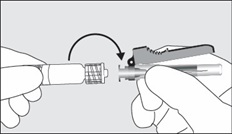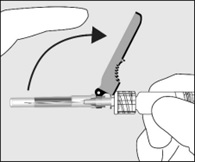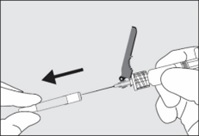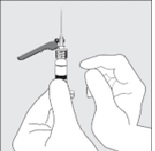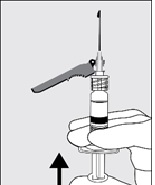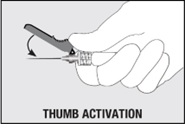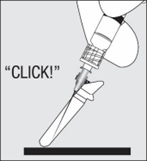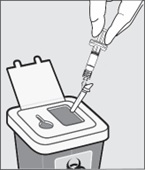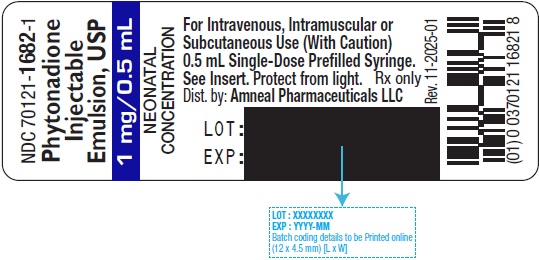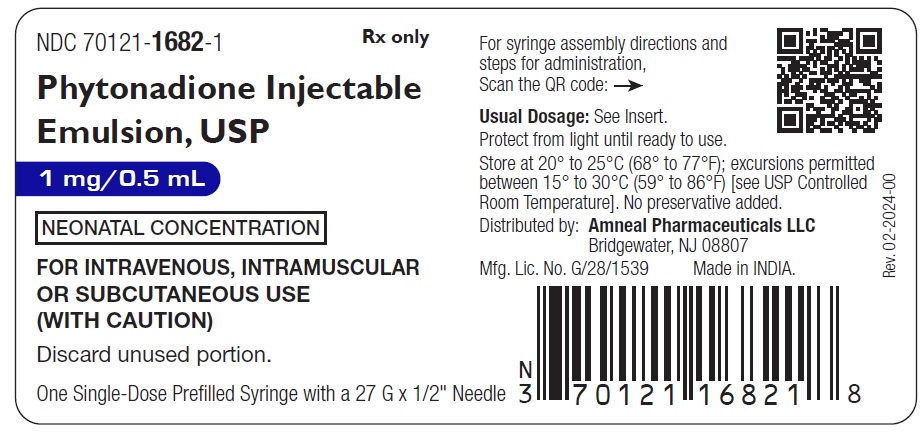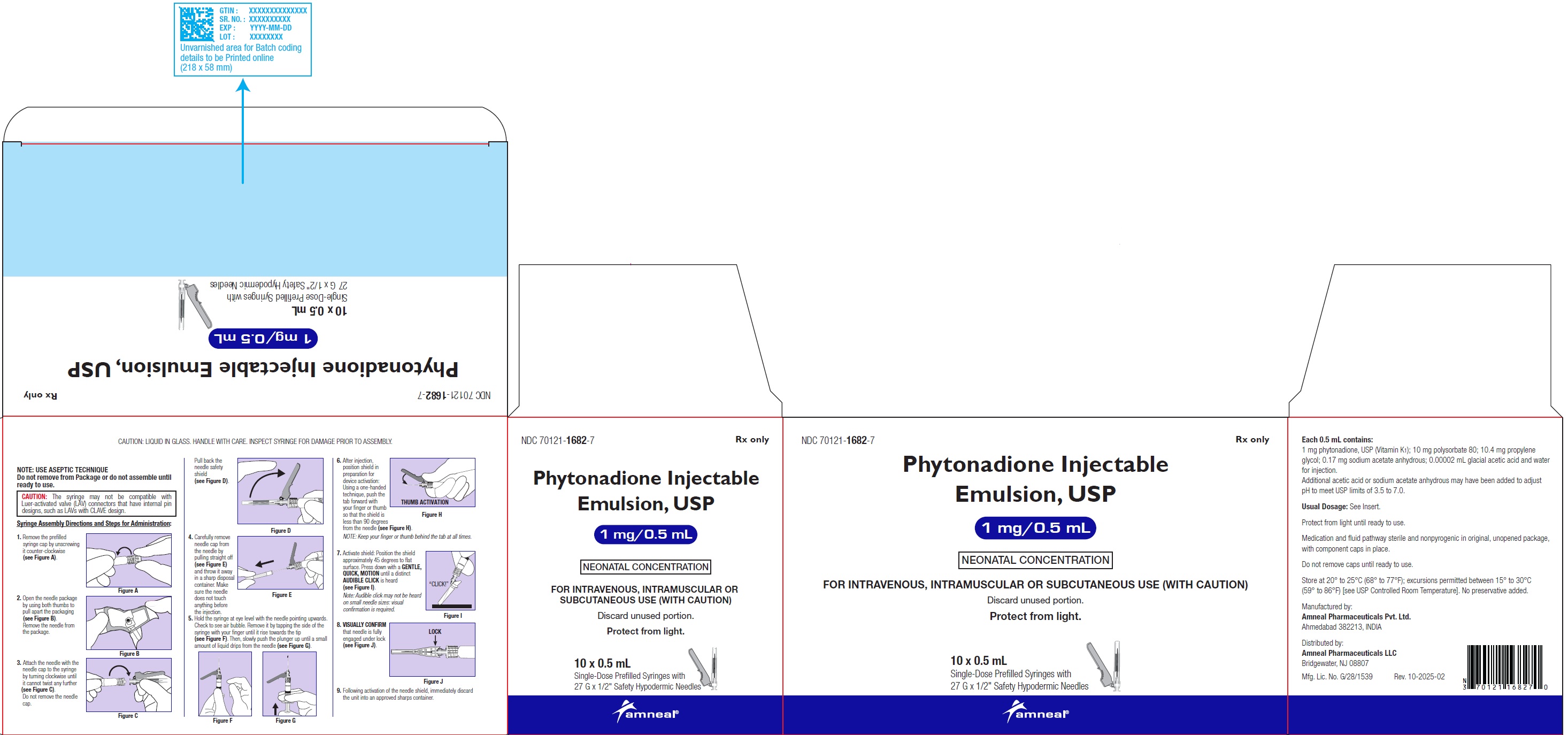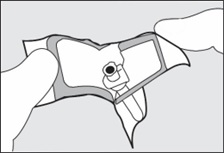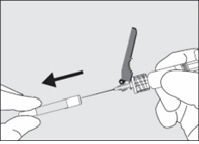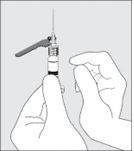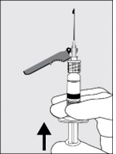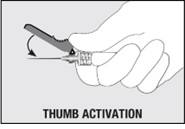 DRUG LABEL: phytonadione
NDC: 70121-1682 | Form: INJECTION, EMULSION
Manufacturer: Amneal Pharmaceuticals LLC
Category: prescription | Type: HUMAN PRESCRIPTION DRUG LABEL
Date: 20251023

ACTIVE INGREDIENTS: PHYTONADIONE 1 mg/0.5 mL
INACTIVE INGREDIENTS: POLYSORBATE 80; PROPYLENE GLYCOL; SODIUM ACETATE ANHYDROUS; ACETIC ACID; WATER

HIGHLIGHTS OF PRESCRIBING INFORMATION

These highlights do not include all the information needed to use PHYTONADIONE INJECTABLE EMULSION safely and effectively. See full prescribing information for PHYTONADIONE INJECTABLE EMULSION.
PHYTONADIONE injectable emulsion, for intravenous, intramuscular and subcutaneous use.
Initial U.S. Approval: 1960

WARNING – HYPERSENSITIVITY REACTIONS WITH INTRAVENOUS AND INTRAMUSCULAR USE

See full prescribing information for complete boxed warning.

Fatal hypersensitivity reactions, including anaphylaxis, have occurred during and immediately after INTRAVENOUS and INTRAMUSCULAR injection of phytonadione injectable emulsion. Reactions have occurred despite dilution to avoid rapid infusion and upon first and subsequent doses. Avoid the intravenous and intramuscular routes of administration unless the subcutaneous route is not feasible and the serious risk is justified. (5.1)

1 INDICATIONS AND USAGE

Phytonadione injectable emulsion is a vitamin K replacement indicated for the treatment of the following coagulation disorders which are due to faulty formation of factors II, VII, IX and X when caused by vitamin K deficiency or interference with vitamin K activity.

- Anticoagulant-induced hypoprothrombinemia deficiency caused by coumarin or indanedione derivatives. (1.1)
- Hypoprothrombinemia due to antibacterial therapy. (1.1)
- Hypoprothrombinemia secondary to factors limiting absorption or synthesis of vitamin K, e.g., obstructive jaundice, biliary fistula, sprue, ulcerative colitis, celiac disease, intestinal resection, cystic fibrosis of the pancreas and regional enteritis. (1.1)
- Other drug-induced hypoprothrombinemia where it is definitely shown that the result is due to interference with vitamin K metabolism, e.g., salicylates. (1.1)

Phytonadione injectable emulsion is indicated for prophylaxis and treatment of vitamin K-deficiency bleeding in neonates. (1.2)

2 DOSAGE AND ADMINISTRATION

- Administer phytonadione injectable emulsion by the subcutaneous route, whenever possible. (2.1)
- When intravenous administration is unavoidable, inject the drug very slowly, not exceeding 1 mg per minute. (2.1)

3 DOSAGE FORMS AND STRENGTHS

Injection: 1 mg/0.5 mL in a single-dose Pre-Filled Glass Syringe. (3)

4 CONTRAINDICATIONS

Hypersensitivity to any component of this medication. (4)

5 WARNINGS AND PRECAUTIONS

- Cutaneous Reactions: May occur with parenteral use. Discontinue drug and manage medically. (5.3)

6 ADVERSE REACTIONS

Most common adverse reactions are cyanosis, diaphoresis, dizziness, dysgeusia, dyspnea, flushing, hypotension and tachycardia. (6)

To report SUSPECTED ADVERSE REACTIONS, contact Amneal Pharmaceuticals LLC at 1-877-835-5472 or FDA at 1-800-FDA-1088 or www.fda.gov/medwatch.

7 DRUG INTERACTIONS

Anticoagulants: May induce temporary resistance to prothrombin-depressing anticoagulants. (7)

8 USE IN SPECIFIC POPULATIONS

- Pregnancy: If available, use the preservative-free formulation in pregnant women. (8.1)
- Lactation: If available, use the preservative-free formulation in lactating women. (8.2)
- Pediatric Use: The safety and effectiveness of phytonadione injectable emulsion in pediatric patients from 6 months to 17 years have not been established. (8.4)

FULL PRESCRIBING INFORMATION

WARNING – HYPERSENSITIVITY REACTIONS WITH INTRAVENOUS AND INTRAMUSCULAR USE

Fatal hypersensitivity reactions, including anaphylaxis, have occurred during and immediately after intravenous and intramuscular injection of phytonadione injectable emulsion. Reactions have occurred despite dilution to avoid rapid intravenous infusion and upon first dose. Avoid the intravenous and intramuscular routes of administration unless the subcutaneous route is not feasible and the serious risk is justified [see Warnings and Precautions (5.1)].

1 INDICATIONS AND USAGE

1.1 Treatment of Hypoprothrombinemia Due to Vitamin K Deficiency or Interference

Phytonadione injectable emulsion is indicated for the treatment of the following coagulation disorders which are due to faulty formation of factors II, VII, IX and X when caused by vitamin K deficiency or interference with vitamin K activity:

- Anticoagulant-induced hypoprothrombinemia caused by coumarin or indanedione derivatives.
- Hypoprothrombinemia due to antibacterial therapy.
- Hypoprothrombinemia secondary to factors limiting absorption or synthesis of vitamin K, e.g., obstructive jaundice, biliary fistula, sprue, ulcerative colitis, celiac disease, intestinal resection, cystic fibrosis of the pancreas and regional enteritis.
- Other drug-induced hypoprothrombinemia where it is definitely shown that the result is due to interference with vitamin K metabolism, e.g., salicylates.

1.2 Prophylaxis and Treatment of Vitamin K-Deficiency Bleeding in Neonates

Phytonadione injectable emulsion is indicated for prophylaxis and treatment of vitamin K-deficiency bleeding in neonates.

2 DOSAGE AND ADMINISTRATION

2.1 Dosing Considerations

Whenever possible, administer phytonadione injectable emulsion by the subcutaneous route [see Boxed Warning]. When intravenous administration is unavoidable, inject the drug very slowly, not exceeding 1 mg per minute [see Warnings and Precautions (5.1)].

Monitor international normalized ratio (INR) regularly and as clinical conditions indicate. Use the lowest effective dose of phytonadione injectable emulsion.

The coagulant effects of phytonadione injectable emulsion are not immediate; improvement of INR may take 1 hour to 8 hours. Interim use of whole blood or component therapy may also be necessary if bleeding is severe.

When phytonadione injectable emulsion is used to correct excessive anticoagulant-induced hypoprothrombinemia, anticoagulant therapy still being indicated, the patient is again faced with the clotting hazards existing prior to starting the anticoagulant therapy. Phytonadione is not a clotting agent, but overzealous therapy with phytonadione injectable emulsion may restore conditions which originally permitted thromboembolic phenomena. Dosage should be kept as low as possible and INR should be checked regularly as clinical conditions indicate.

2.2 Recommended Dosage for Coagulation Disorders from Vitamin K Deficiency or Interference

The recommended dosage of phytonadione injectable emulsion is based on whether the hypoprothrombinemia is anticoagulant-induced (e.g., due to coumarin or indanedione derivatives) or non-anticoagulant-induced (e.g., due to antibiotics; salicylates or other drugs; factors limiting absorption or synthesis) as follows:

- Anticoagulant-Induced Hypoprothrombinemia: Phytonadione injectable emulsion 2.5 mg to 10 mg or more subcutaneously, intramuscularly, or intravenously. Up to 25 mg to 50 mg may be administered as a single-dose.
  Repeated large doses of phytonadione injectable emulsion are not warranted in liver disease if the initial response is unsatisfactory. Failure to respond to phytonadione injectable emulsion may indicate that the condition being treated is inherently unresponsive to phytonadione injectable emulsion.
- Hypoprothrombinemia Due to Other Causes (Non-Anticoagulation-Induced Hypoprothrombinemia): Phytonadione injectable emulsion 2.5 mg to 25 mg or more intravenously, intramuscularly, or subcutaneously. Up to 50 mg may be administered as a single-dose.

Evaluate INR after 6 hours to 8 hours and repeat dose if INR remains prolonged. Modify subsequent dosage (amount and frequency) based on the INR or clinical condition.

2.3 Recommended Dosage for Prophylaxis and Treatment of Vitamin K Deficiency Bleeding in Neonates

Prophylaxis of Vitamin K-Deficiency Bleeding in Neonates

The recommended dosage of phytonadione injectable emulsion is 0.5 mg to 1 mg within one hour of birth for a single-dose.

Treatment of Vitamin K-Deficiency Bleeding in Neonates

The recommended dosage of phytonadione injectable emulsion is 1 mg given either subcutaneously or intramuscularly. Consider higher doses if the mother has been receiving oral anticoagulants.

A failure to respond (shortening of the INR in 2 hours to 4 hours) may indicate another diagnosis or coagulation disorder.

2.4 Directions for Dilution

CAUTION: The syringe may not be compatible with Luer-activated valve (LAV) connectors that have internal pin designs, such as LAVs with CLAVE design.

Dilute phytonadione injectable emulsion with 0.9% Sodium Chloride Injection, 5% Dextrose Injection, or 5% Dextrose and Sodium Chloride Injection.

When diluted, start administration of phytonadione injectable emulsion immediately after dilution.

Discard unused portions of diluted solution as well as unused contents of the syringe.

Protect phytonadione injectable emulsion from light at all times.

Parenteral drug products should be inspected visually for particulate matter and discoloration prior to administration, whenever solution and container permit.

3 DOSAGE FORMS AND STRENGTHS

Injection: 1 mg/0.5 mL in a single-dose Pre-Filled Glass Syringe.

4 CONTRAINDICATIONS

Hypersensitivity to phytonadione or any other component of this medication [see Warnings and Precautions (5.1)].

5 WARNINGS AND PRECAUTIONS

5.1 Hypersensitivity Reactions

Fatal and severe hypersensitivity reactions, including anaphylaxis, have occurred with intravenous or intramuscular administration of phytonadione injectable emulsion. Reactions have occurred despite dilution to avoid rapid intravenous infusion and upon first dose. These reactions have included shock, cardiorespiratory arrest, flushing, diaphoresis, chest pain, tachycardia, cyanosis, weakness and dyspnea. Administer phytonadione injectable emulsion subcutaneously whenever feasible. Avoid the intravenous and intramuscular routes of administration unless the subcutaneous route is not feasible and the serious risk is justified [see Dosage and Administration (2.1)].

5.3 Cutaneous Reactions

Parenteral administration of vitamin K replacements (including phytonadione injectable emulsion) may cause cutaneous reactions. Reactions have included eczematous reactions, scleroderma-like patches, urticaria and delayed-type hypersensitivity reactions. Time of onset ranged from 1 day to a year after parenteral administration. Discontinue phytonadione injectable emulsion for skin reactions and institute medical management.

6 ADVERSE REACTIONS

The following serious adverse reactions are described elsewhere in the labeling:

- Hypersensitivity Reactions [see Warnings and Precautions (5.1)]
- Cutaneous Reactions [see Warnings and Precautions (5.3)]

6.1 Clinical Trials and Post-Marketing Experience

Because clinical trials are conducted under widely varying conditions, adverse reaction rates observed in the clinical trials of a drug cannot be directly compared to rates in the clinical trials of another drug and may not reflect the rates observed in practice.

The following adverse reactions have been identified during post-approval use of phytonadione injectable emulsion. Because these reactions were reported voluntarily from a population of uncertain size, it is not always possible to reliably estimate their frequency or establish a causal relationship to drug exposure.

Cardiac Disorders: Tachycardia, hypotension.

General disorders and administration site conditions: Generalized flushing; pain, swelling and tenderness at injection site.

Hepatobiliary Disorders: Hyperbilirubinemia.

Immune System Disorders: Fatal hypersensitivity reactions, anaphylactic reactions.

Neurologic: Dysgeusia, dizziness.

Pulmonary: Dyspnea.

Skin and Subcutaneous Tissue Disorders: Erythema, pruritic plaques, scleroderma-like lesions, erythema perstans.

Vascular: Cyanosis.

7 DRUG INTERACTIONS

Anticoagulants

Phytonadione injectable emulsion may induce temporary resistance to prothrombin-depressing anticoagulants, especially when larger doses of phytonadione injectable emulsion are used. Should this occur, higher doses of anticoagulant therapy may be needed when resuming anticoagulant therapy, or a change in therapy to a different class of anticoagulant may be necessary (i.e., heparin sodium).

Phytonadione injectable emulsion does not affect the anticoagulant action of heparin.

8 USE IN SPECIFIC POPULATIONS

8.1 Pregnancy

Risk Summary

If phytonadione is needed during pregnancy, consider using a preservative-free formulation.

Published studies with the use of phytonadione during pregnancy have not reported a clear association with phytonadione and adverse developmental outcomes (see Data). There are maternal and fetal risks associated with vitamin K deficiency during pregnancy (see Clinical Considerations). Animal reproduction studies have not been conducted with phytonadione.

The estimated background risk for the indicated population is unknown. All pregnancies have a background risk of birth defect, loss, or other adverse outcomes. In the U.S. general population, the estimated background risk of major birth defects and miscarriage in clinically recognized pregnancies is 2% to 4% and 15% to 20%, respectively.

Clinical Considerations

Disease-associated maternal and/or embryo/fetal risk

Pregnant women with vitamin K deficiency hypoprothrombinemia may be at an increased risk for bleeding diatheses during pregnancy and hemorrhagic events at delivery. Subclinical maternal vitamin K deficiency during pregnancy has been implicated in rare cases of fetal intracranial hemorrhage.

Data

Human Data

Phytonadione has been measured in cord blood of infants whose mothers were treated with phytonadione during pregnancy in concentrations lower than seen in maternal plasma. Administration of vitamin K1 to pregnant women shortly before delivery increased both maternal and cord blood concentrations. Published data do not report a clear association with phytonadione and adverse maternal or fetal outcomes when used during pregnancy. However, these studies cannot definitively establish the absence of any risk because of methodologic limitations including small sample size and lack of blinding.

Animal Data

In pregnant rats receiving vitamin K1 orally, fetal plasma and liver concentrations increased following administration, supporting placental transfer.

8.2 Lactation

Risk Summary

If available, preservative-free phytonadione injectable emulsion is recommended when phytonadione injectable emulsion is needed during lactation [see Use in Specific Populations (8.4)].

Phytonadione is present in breastmilk. There are no data on the effects of phytonadione injectable emulsion on the breastfed child or on milk production. The developmental and health benefits of breastfeeding should be considered along with the clinical need for phytonadione injectable emulsion and any potential adverse effects on the breastfed child from phytonadione injectable emulsion or from the underlying maternal condition.

8.4 Pediatric Use

The safety and effectiveness of phytonadione injectable emulsion for prophylaxis and treatment of vitamin K deficiency have been established in neonates. Use of phytonadione injection for prophylaxis and treatment of vitamin K deficiency is based on published clinical studies.

10 OVERDOSAGE

Hemolysis, jaundice and hyperbilirubinemia in newborns, particularly in premature infants, may result from phytonadione injectable emulsion overdose.

11 DESCRIPTION

Phytonadione, USP is a vitamin K replacement, which is a clear, yellow to amber, very viscous liquid. It is soluble in dehydrated alcohol, in benzene, in chloroform, in ether and in vegetable oils; slightly soluble in alcohol and insoluble in water. It has a molecular weight of 450.70 g/mol.

Phytonadione is 2-Methyl-3-(3,7,11,15-tetramethylhexadec-2-en-1-yl)naphthalene-1,4-dione. Its molecular formula is C31H46O2 and its molecular structure is:

Phytonadione Injectable Emulsion, USP is a sterile, clear yellow color solution of vitamin K1, with a pH of 3.5 to 7.0, available for injection by the intravenous, intramuscular and subcutaneous routes. Phytonadione injectable emulsion, USP is available in 1 mg (1 mg/0.5 mL) single-dose prefilled glass syringe.

Each 0.5 mL of Phytonadione Injectable Emulsion, USP contains:

Active:

Phytonadione, USP (Vitamin K1)………………1 mg

Inactive:

Polysorbate 80 …………………………10 mg

Propylene glycol ………………………10.4 mg

Sodium acetate anhydrous.…………..…0.17 mg

Glacial acetic acid .………….….….......0.00002 mL

Water for injection.….…………………q.s. to 0.5 mL

Additional glacial acetic acid or sodium acetate anhydrous may have been added to adjust pH to meet USP limits of 3.5 to 7.0.

12 CLINICAL PHARMACOLOGY

12.1 Mechanism of Action

Phytonadione injectable emulsion aqueous colloidal solution of vitamin K1 for parenteral injection, possesses the same type and degree of activity as does naturally-occurring vitamin K, which is necessary for the production via the liver of active prothrombin (factor II), proconvertin (factor VII), plasma thromboplastin component (factor IX) and Stuart factor (factor X). Vitamin K is an essential cofactor for a microsomal enzyme that catalyzes the post-translational carboxylation of multiple, specific, peptide-bound glutamic acid residues in inactive hepatic precursors of factors II, VII, IX and X. The resulting gamma-carboxy-glutamic acid residues convert the precursors into active coagulation factors that are subsequently secreted by liver cells into the blood.

In normal animals and humans, phytonadione is virtually devoid of activity. However, in animals and humans deficient in vitamin K, the pharmacological action of vitamin K is related to its normal physiological function, that is, to promote the hepatic biosynthesis of vitamin K dependent clotting factors.

12.2 Pharmacodynamics

The action of the aqueous dispersion, when administered intravenously, is generally detectable within an hour or two and hemorrhage is usually controlled within 3 hours to 6 hours. A normal INR may often be obtained in 12 hours to 14 hours.

12.3 Pharmacokinetics

Absorption:

Phytonadione is readily absorbed following intramuscular administration.

Distribution:

After absorption, phytonadione is initially concentrated in the liver, but the concentration declines rapidly. Very little vitamin K accumulates in tissues.

Elimination:

Little is known about the metabolic fate of vitamin K. Almost no free unmetabolized vitamin K appears in bile or urine.

13 NONCLINICAL TOXICOLOGY

13.1 Carcinogenesis, Mutagenesis, Impairment of Fertility

Studies of carcinogenicity, genotoxicity or impairment of fertility have not been conducted with phytonadione.

16 HOW SUPPLIED/STORAGE AND HANDLING

Phytonadione Injectable Emulsion USP, 1 mg/0.5 mL is available as clear yellow color, solution filled in prefilled glass syringe with SRC tip cap, assembled with grey plunger stopper and natural plunger rod. It is supplied in carton containing ten plastic trays, each having one single-dose prefilled glass syringes and one, SurGuard® 3 safety hypodermic 27 G. x 1/2” needle with the following presentations:

Unit of Sale | Strength | Each
NDC 70121-1682-7; (Carton of 10) | 1 mg/0.5 mL | NDC 70121-1682-1; (0.5 mL prefilled syringe)

Store at 20° to 25°C (68° to 77°F); excursions permitted between 15° to 30°C (59° to 86°F) [see USP Controlled Room Temperature].

Protect phytonadione injectable emulsion from light. Store container in closed original carton until contents have been used.

Syringe Assembly Directions:

See User Guide

USE ASEPTIC TECHNIQUE

Do not remove from carton or assemble until ready to use.

CAUTION: The syringe may not be compatible with Luer-activated valve (LAV) connectors that have internal pin designs, such as LAVs with CLAVE design.

1. Remove the prefilled syringe cap by unscrewing it counter-clockwise (see Figure A).

Figure A

2. Open the needle package by using both thumbs to pull apart the packaging (see Figure B). Remove the needle from the package.

Figure B

3. Attach the needle with the needle cap to the syringe by turning clockwise until it cannot twist any further (see Figure C). Do not remove the needle cap.

Figure C

Pull back the needle safety shield (see Figure D).

Figure D

4. Carefully remove needle cap from the needle by pulling straight off (see Figure E) and throw it away in a sharp disposal container. Make sure the needle does not touch anything before the injection.

Figure E

5. Hold the syringe at eye level with the needle pointing upwards. Check to see air bubble. Remove it by tapping the side of the syringe with your finger until it rise towards the tip (see Figure F). Then, slowly push the plunger up until a small amount of liquid drips from the needle (see Figure G).

Figure F

Figure G

6. After injection, position shield in preparation for device activation: Using a one-handed technique, push the tab forward with your finger or thumb so that the shield is less than 90 degrees from the needle (see Figure H).

NOTE: Keep your finger or thumb behind the tab at all times.

Figure H

7. Activate shield: Position the shield approximately 45 degrees to flat surface. Press down with a GENTLE, QUICK, MOTION until a distinct AUDIBLE CLICK is heard (see Figure I).

Note: Audible click may not be heard on small needle sizes: visual confirmation is required.

Figure I

8. VISUALLY CONFIRM that needle is fully engaged under lock (see Figure J).

Figure J

9. Following activation of the needle shield, immediately discard the unit into an approved sharps container.

CAUTION: LIQUID IN GLASS. HANDLE WITH CARE. INSPECT SYRINGE FOR DAMAGE PRIOR TO ASSEMBLY.

17 PATIENT COUNSELING INFORMATION

Inform the patient of the following important risks of phytonadione injectable emulsion:

Serious Hypersensitivity Reactions

Advise the patient and caregivers to immediately report signs of hypersensitivity after receiving phytonadione injectable emulsion [see Warnings and Precautions (5.1)].

Cutaneous Reactions

Advise the patient and caregivers to report the occurrence of new rashes after receiving phytonadione injectable emulsion. These reactions may be delayed for up to a year after treatment [see Warnings and Precautions (5.3)].

Manufactured by:

Amneal Pharmaceuticals Pvt. Ltd.

Ahmedabad 382213, INDIA

Distributed by:

Amneal Pharmaceuticals LLC

Bridgewater, NJ 08807

Rev. 11-2025-03

USER GUIDE

Phytonadione Injectable Emulsion, USP

1 mg/0.5 mL

NOTE: USE ASEPTIC TECHNIQUE

Do not remove from Package or do not assemble until ready to use.

CAUTION: The syringe may not be compatible with Luer-activated valve (LAV) connectors that have internal pin designs, such as LAVs with CLAVE design.

Package Contents:

- A Pre-filled Glass Syringe containing Phytonadione Injectable Emulsion
- A SURGUARD® 3 SAFETY HYPODERMIC NEEDLE

Syringe Assembly Directions and Steps for Administration:

1. Remove the Phytonadione Injectable Emulsion tray from carton. Open the tray and take out prefilled glass syringe (see Figure A).

Figure A

2. Remove the prefilled syringe cap by unscrewing it counter-clockwise (see Figure B).

Figure B

3. Open the needle package by using both thumbs to pull apart the packaging (see Figure C). Remove the needle from the package.

Figure C

4. Attach the needle with the needle cap to the syringe by turning clockwise until it cannot twist any further (see Figure D). Do not remove the needle cap.

Pull back the needle safety shield (see Figure E).

Figure D

Figure E

5. Carefully remove needle cap from the needle by pulling straight off (see Figure F) and throw it away in a sharp disposal container. Make sure the needle does not touch anything before the injection.

Figure F

6. Hold the syringe at eye level with the needle pointing upwards.

Check to see air bubble. Remove it by tapping the side of the syringe with your finger until it rise towards the tip (see Figure G).

Then, slowly push the plunger up until a small amount of liquid drips from the needle (see Figure H).

Figure G

Figure H

7. After injection, position shield in preparation for device activation: Using a one-handed technique, push the tab forward with your finger or thumb so that the shield is less than 90 degrees from the needle (see Figure I).

NOTE: Keep your finger or thumb behind the tab at all times.

Figure I

8. Activate shield: Position the shield approximately 45 degrees to flat surface. Press down with a GENTLE, QUICK, MOTION until a distinct AUDIBLE CLICK is heard (see Figure J).

Note: Audible click may not be heard on small needle sizes: visual confirmation is required.

Figure J

9. VISUALLY CONFIRM that needle is fully engaged under lock (see Figure K).

Figure K

10. Following activation of the needle shield, immediately discard the unit into an approved sharps container (see Figure L).

Figure L

CAUTION: LIQUID IN GLASS. HANDLE WITH CARE. INSPECT SYRINGE FOR DAMAGE PRIOR TO ASSEMBLY.

For more information, go to www.amneal.com or call Amneal Pharmaceuticals LLC at 1-877-835-5472.

Manufactured by:

Amneal Pharmaceuticals Pvt. Ltd.

Ahmedabad 382213, INDIA

Distributed by:

Amneal Pharmaceuticals LLC

Bridgewater, NJ 08807

Rev. 10-2025-02

PRINCIPAL DISPLAY PANEL

NDC 70121-1682-1

Phytonadione Injectable Emulsion USP, 1 mg/0.5 mL

0.5 mL Prefilled Syringe Label

Rx only

Amneal Pharmaceuticals LLC

NDC 70121-1682-1

Phytonadione Injectable Emulsion USP, 1 mg/0.5 mL

0.5 mL Tray Label

Rx only

Amneal Pharmaceuticals LLC

NDC 70121-1682-7

Phytonadione Injectable Emulsion USP, 1 mg/0.5 mL

10 x 0.5 mL Carton Label

Rx only

Amneal Pharmaceuticals LLC